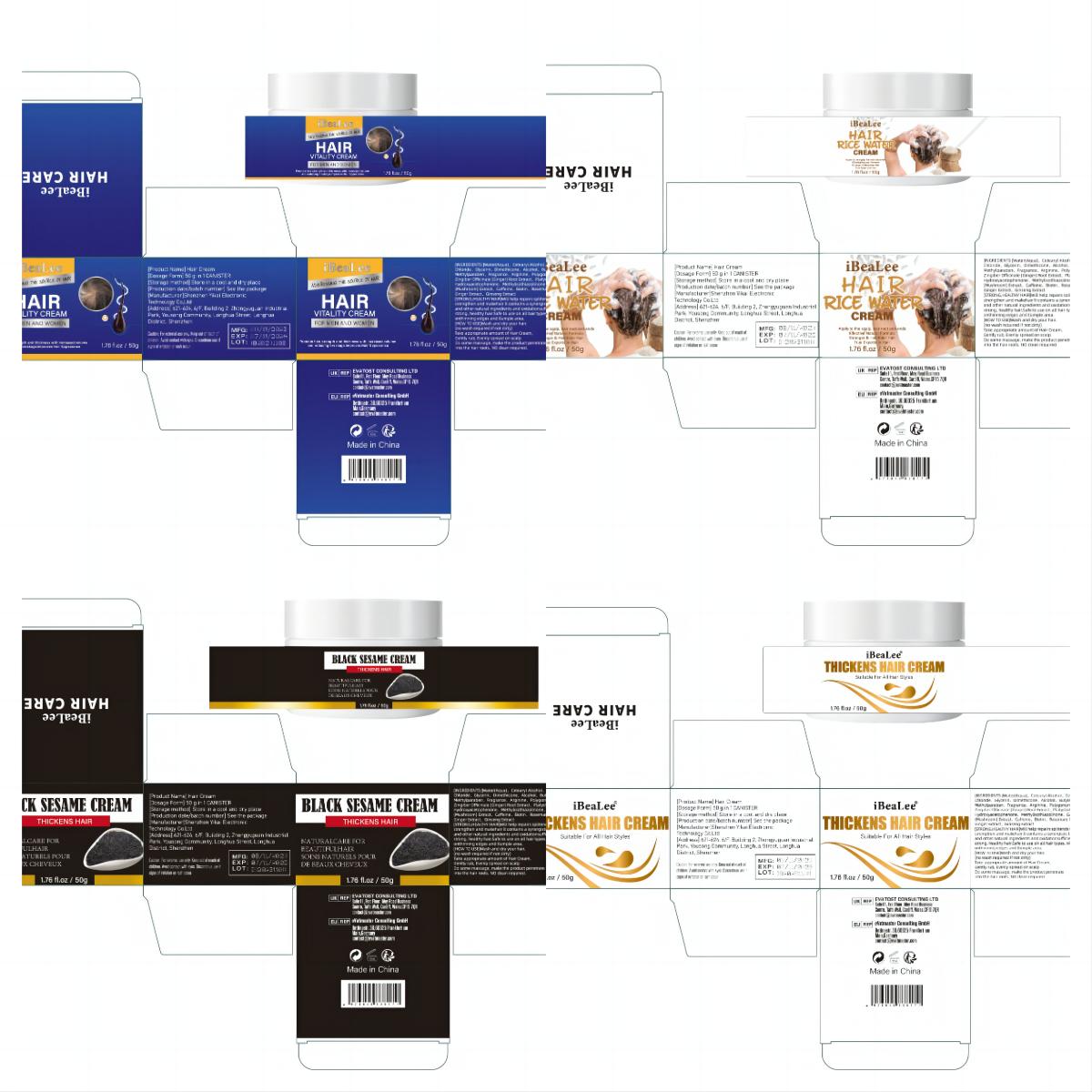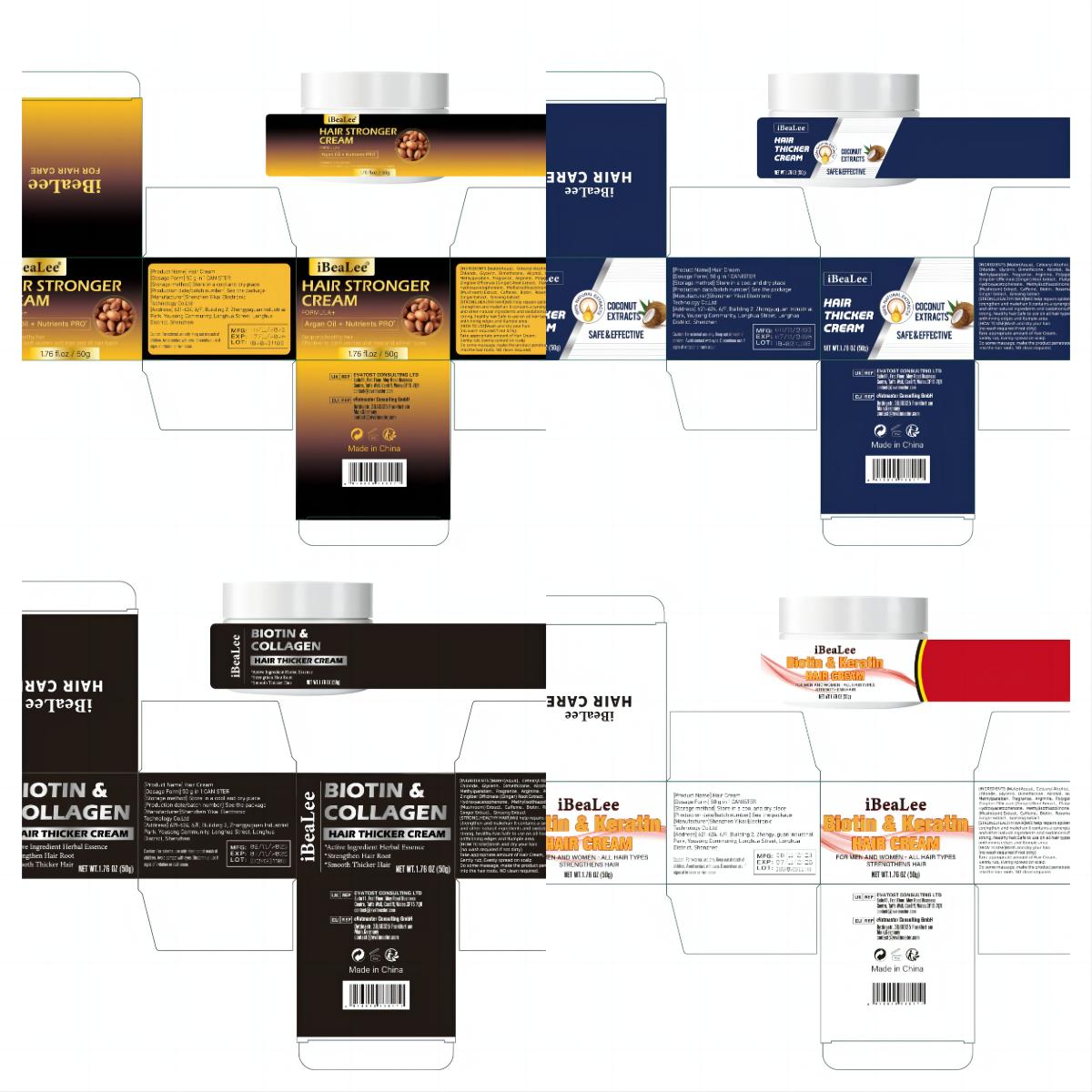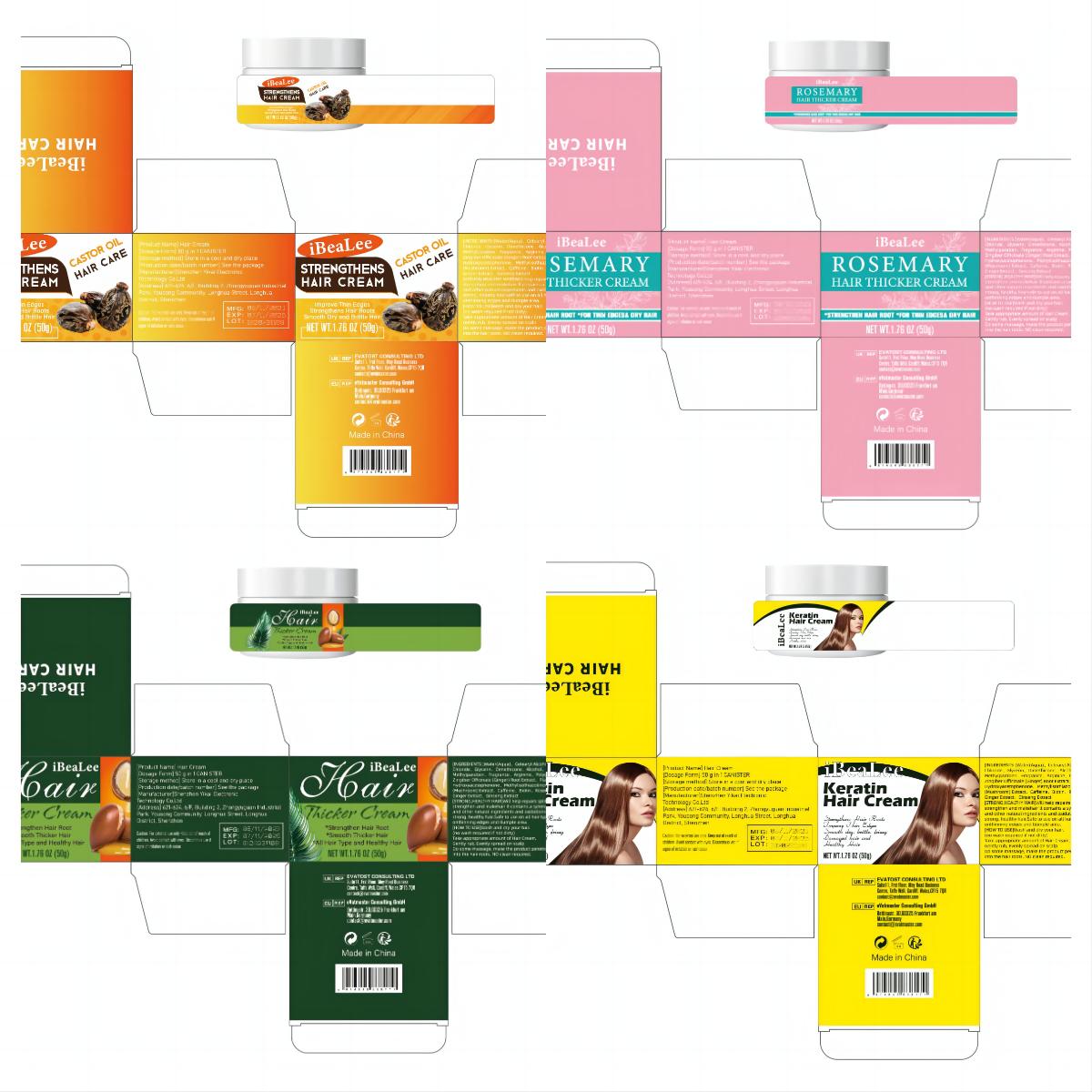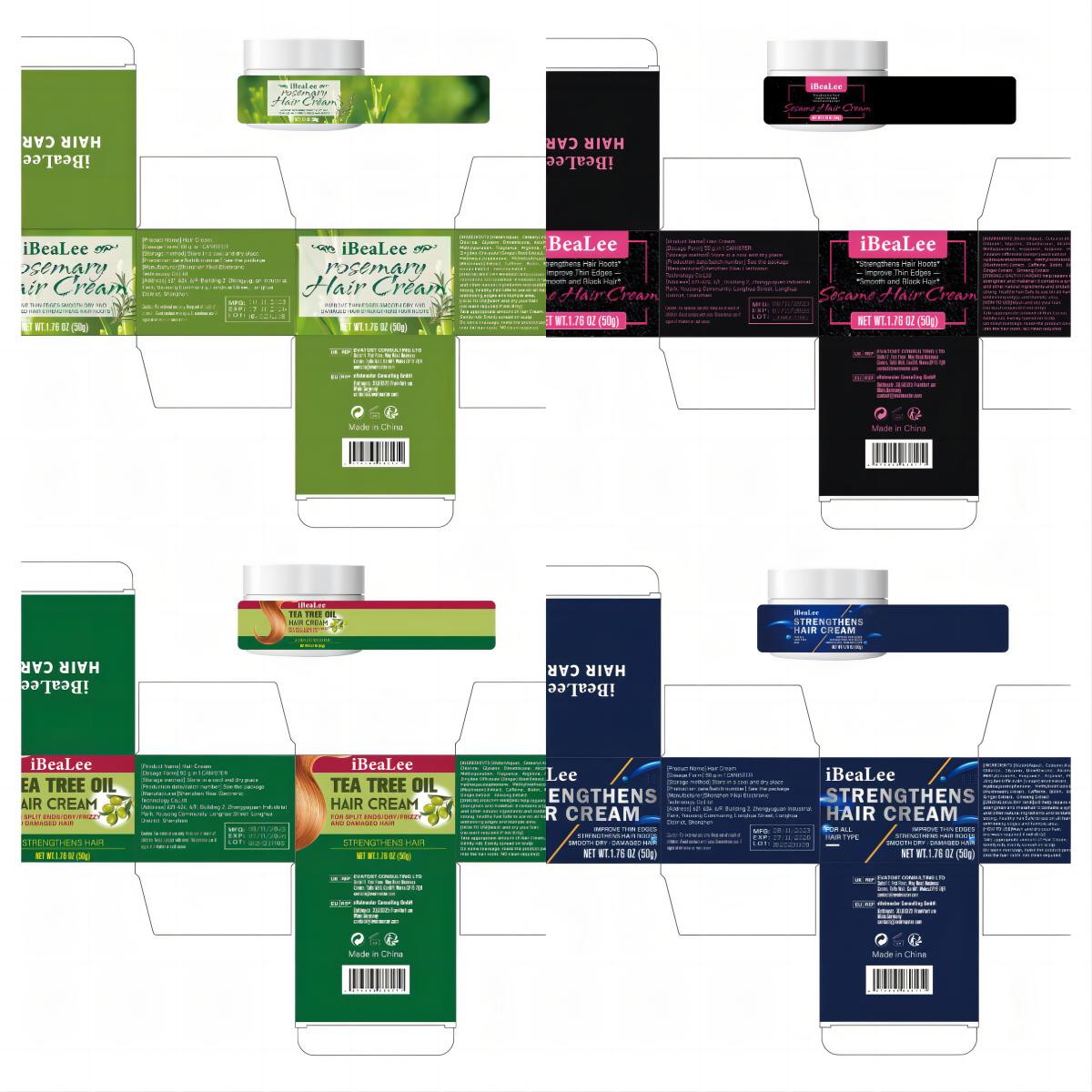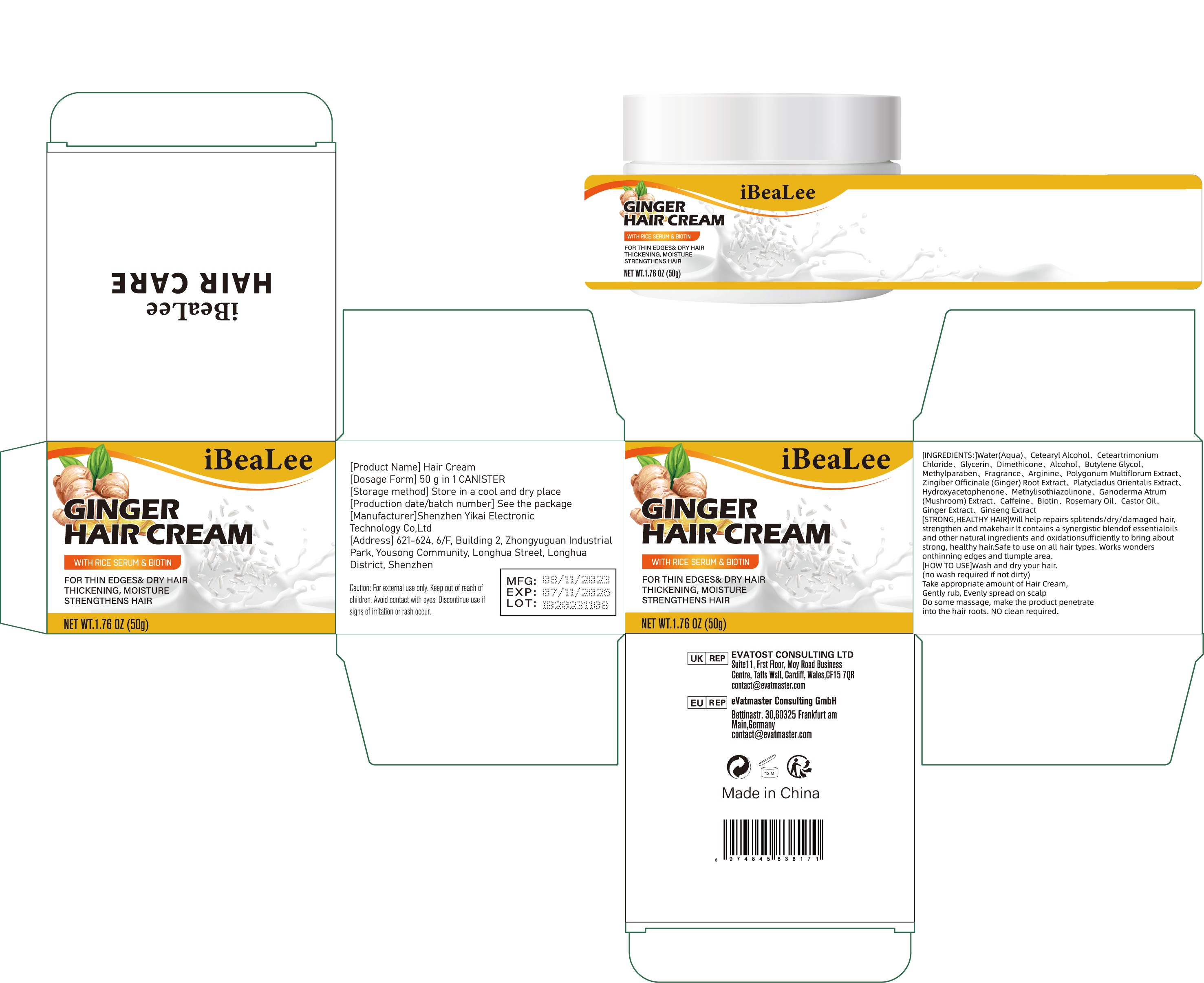 DRUG LABEL: Hair Cream
NDC: 83809-010 | Form: CREAM
Manufacturer: Shenzhen Yikai Electronic Technology Co., Ltd.
Category: otc | Type: HUMAN OTC DRUG LABEL
Date: 20231208

ACTIVE INGREDIENTS: BIOTIN 0.1 g/100 g
INACTIVE INGREDIENTS: POLYGONATUM MULTIFLORUM ROOT; HYDROXYACETOPHENONE; ASIAN GINSENG; CASTOR OIL; PLATYCLADUS ORIENTALIS LEAF; CAFFEINE; METHYLPARABEN; CETEARTRIMONIUM CHLORIDE; FRAGRANCE 13576; ARGININE; WATER; ALCOHOL; GINGER; METHYLISOTHIAZOLINONE; GLYCERIN; BUTYLENE GLYCOL; DIMETHICONE; CETOSTEARYL ALCOHOL; REISHI; ROSEMARY OIL

010-001

Active Ingredient

Biotin 0.1%

Purpose

Hair Regrowth Treatments

Use

[STRONG,HEALTHY HAIR]Will help repairs splitends/dry/damaged hair,
strengthen and makehair lt contains a synergistic blendof essentialoils
and other natural ingredients and oxidationsufficiently to bring about
strong, healthy hair.Safe to use on all hair types. Works wonders
onthinning edges and tlumple area.

Warnings

For external use only. Keep out of reach of
children. Avoid contact with eyes. Discontinue use if
signs of iritation or rash occur.

Stop Use

This product has not been found allergic. If allergic occurs, stop using it immediately.

Keep Oot Of Reach Of Children

Please store this product out of the reach of children

Directions

[HOW TO USE]Wash and dry your hair.
(no wash required if not dirty)
Take appropriate amount of Hair Cream,
Gently rub, Evenly spread on scalp
Do some massage, make the product penetrate
into the hair roots. NO clean required.

Inactive ingredients

Water(Aqua), Cetearyl Alcohol, Ceteartrimonium Chloride, Glycerin, Dimethicone, Alcohol, Butylene Glycol, Methylparaben, Fragrance, Arginine, Polygonum Multiflorum Extract, Zingiber Officinale (Ginger) Root Extract, Platycladus Orientalis Extract, Hydroxyacetophenone, Methylisothiazolinone, Ganoderma Atrum (Mushroom) Extract, Caffeine, Rosemary Oil, Castor Oil, Ginger Extract, Ginseng Extrac